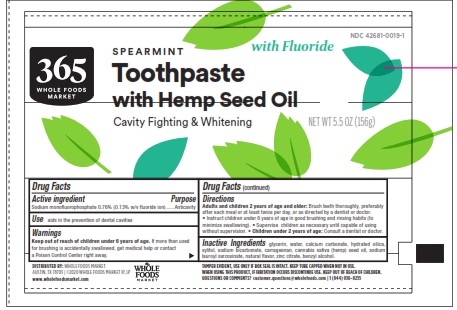 DRUG LABEL: Spearmint Whitening with Hemp Oil
NDC: 42681-0019 | Form: PASTE, DENTIFRICE
Manufacturer: Whole Foods
Category: otc | Type: HUMAN OTC DRUG LABEL
Date: 20251113

ACTIVE INGREDIENTS: SODIUM MONOFLUOROPHOSPHATE 0.13 g/100 g
INACTIVE INGREDIENTS: CANNABIS SATIVA SEED OIL; SODIUM LAUROYL SARCOSINATE; BENZYL ALCOHOL; ZINC CITRATE; SODIUM BICARBONATE; XYLITOL; CALCIUM CARBONATE; WATER; GLYCERIN; CARRAGEENAN; HYDRATED SILICA

5820030 Cavity Fighting & Whitening F with Hemp

Active ingredient Purpose

Sodium monofluorophosphate 0.76% (0.13% w/v fluoride ion) ...... Anticavity

PURPOSE

INDICATIONS AND USAGE

Use aids in the prevention of dental cavities

WARNINGS

Warnings

Keep out of reach of children under 6 years of age. If more than used for brushing is accidentally swallowed, get medical help or contact a Poison Control Center right away.

Directions

Adults and children 2 years of age and older: Brush teeth thoroughly, preferably after each meal or at least twice per day, or as directed by a dentist or doctor. * Instruct children under 6 years of age in good brushing and rinsing habits (to minimize swallowing). * Supervise children as necessary until capable of using without supervision. * Children under 2 years of age: Consult a dentist or doctor.

INACTIVE INGREDIENT

Inactive Ingredients glycerin, water, calcium carbonate, hydrated silica, xylitol, sodium bicarbonate, carrageenan, cannabis sativa (hemp) seed oil, sodium auroyl sarcosinate, natural flavor, zinc citrate, benzyl alcohol

Principal Display Panel

Spearmint with Fluoride

Toothpaste

with Hemp Seed Oil

Cavity Fighting & Whitening Net wt 5.5 oz (156g)